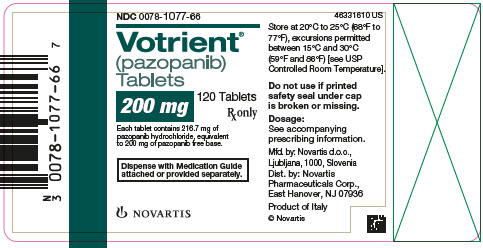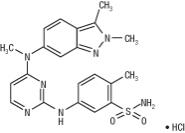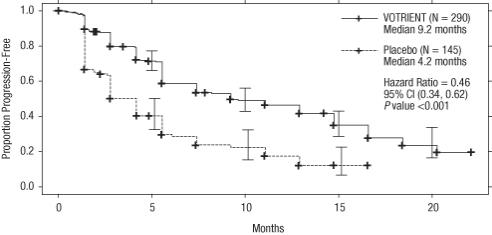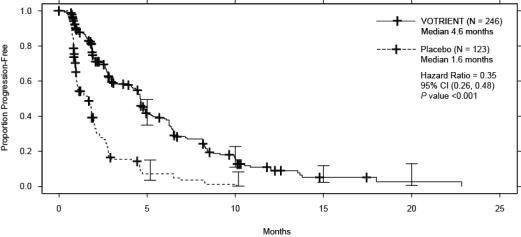 DRUG LABEL: VOTRIENT
NDC: 0078-1077 | Form: TABLET, FILM COATED
Manufacturer: Novartis Pharmaceuticals Corporation
Category: prescription | Type: HUMAN PRESCRIPTION DRUG LABEL
Date: 20251216

ACTIVE INGREDIENTS: PAZOPANIB HYDROCHLORIDE 200 mg/1 1
INACTIVE INGREDIENTS: MAGNESIUM STEARATE; CELLULOSE, MICROCRYSTALLINE; POVIDONE; SODIUM STARCH GLYCOLATE TYPE A POTATO; HYPROMELLOSES; FERROSOFERRIC OXIDE; POLYETHYLENE GLYCOL 400; POLYSORBATE 80; TITANIUM DIOXIDE

HIGHLIGHTS OF PRESCRIBING INFORMATION

These highlights do not include all the information needed to use VOTRIENT safely and effectively. See full prescribing information for VOTRIENT.
VOTRIENT® (pazopanib) tablets, for oral use
Initial U.S. Approval: 2009

WARNING: HEPATOTOXICITY

See full prescribing information for complete boxed warning.

Severe and fatal hepatotoxicity has been observed in clinical trials. Monitor hepatic function and interrupt, reduce, or discontinue dosing as recommended. (5.1)

1 INDICATIONS AND USAGE

VOTRIENT is a kinase inhibitor indicated for the treatment of adults with:

- advanced renal cell carcinoma (RCC). (1.1)
- advanced soft tissue sarcoma (STS) who have received prior chemotherapy. (1.2)

Limitations of Use: The efficacy of VOTRIENT for the treatment of patients with adipocytic soft tissue sarcoma or gastrointestinal stromal tumors has not been demonstrated.

2 DOSAGE AND ADMINISTRATION

- Recommended Dosage: 800 mg orally once daily without food (at least 1 hour before or 2 hours after a meal). (2.1)
- Moderate Hepatic Impairment: 200 mg orally once daily. (2.2)

3 DOSAGE FORMS AND STRENGTHS

Tablets: 200 mg (3)

4 CONTRAINDICATIONS

None. (4)

5 WARNINGS AND PRECAUTIONS

- Hepatic Toxicity: Severe and fatal hepatotoxicity has occurred. Monitor liver tests at baseline, regularly during treatment and as clinically indicated. Withhold VOTRIENT and resume at reduced dose with continued weekly monitoring for 8 weeks, or permanently discontinue with weekly monitoring until resolution based on severity of hepatotoxicity. (2.2, 5.1)
- QT Prolongation and Torsades de Pointes: Monitor patients who are at significant risk of developing QT interval prolongation. Monitor electrocardiograms (ECGs) and electrolytes at baseline and as clinically indicated. Correct hypokalemia, hypomagnesemia, and hypocalcemia prior to initiating VOTRIENT and during treatment. (5.2, 12.2)
- Cardiac Dysfunction: Cardiac dysfunction, including decreased left ventricular ejection fraction (LVEF) and congestive heart failure, have occurred. Monitor blood pressure and manage as appropriate. Monitor for clinical signs or symptoms of congestive heart failure. Conduct baseline and periodic evaluation of LVEF in patients at risk of cardiac dysfunction. Withhold or permanently discontinue VOTRIENT based on severity of cardiac dysfunction. (2.2, 5.3)
- Hemorrhagic Events: Fatal hemorrhagic events have occurred. VOTRIENT has not been studied in patients who have a history of hemoptysis, cerebral hemorrhage, or clinically significant gastrointestinal hemorrhage in the past 6 months. Withhold VOTRIENT and resume at reduced dose or permanently discontinue based on severity of hemorrhagic events. (2.2, 5.4)
- Arterial Thromboembolic Events: Arterial thromboembolic events have been observed and can be fatal. VOTRIENT has not been studied in patients who have had an arterial thromboembolic event within the previous 6 months. Permanently discontinue VOTRIENT in case of an arterial thromboembolic event. (2.2, 5.5)
- Venous Thromboembolic Events: Venous thromboembolic events (VTEs) have been observed, including fatal pulmonary emboli (PE). Monitor for signs and symptoms of VTE and PE. Withhold VOTRIENT and then resume at same dose or permanently discontinue based on severity of VTE. (2.2, 5.6)
- Thrombotic Microangiopathy: Thrombotic microangiopathy (TMA), including thrombotic thrombocytopenic purpura (TTP) and hemolytic uremic syndrome (HUS), has been observed. Permanently discontinue VOTRIENT if TMA occurs. (2.2, 5.7)
- Gastrointestinal Perforation and Fistula: Fatal perforation events have occurred. Monitor for signs and symptoms of gastrointestinal perforation or fistula. Withhold VOTRIENT in case of Grade 2 or 3 gastrointestinal fistula and resume based on medical judgement. Permanently discontinue VOTRIENT in case of gastrointestinal perforation or Grade 4 gastrointestinal fistula. (2.2, 5.8)
- Interstitial Lung Disease/Pneumonitis: Can be fatal. Monitor patients for pulmonary symptoms. Permanently discontinue VOTRIENT in patients who develop interstitial lung disease (ILD) or pneumonitis. (2.2, 5.9)
- Posterior Reversible Encephalopathy Syndrome: Can be fatal. Permanently discontinue VOTRIENT in patients who develop posterior reversible encephalopathy syndrome (PRES). (2.2, 5.10)
- Hypertension: Hypertension, including hypertensive crisis, has been observed. Do not initiate VOTRIENT in patients with uncontrolled hypertension. Optimize blood pressure prior to initiating VOTRIENT. Monitor blood pressure as clinically indicated and initiate and adjust antihypertensive therapy as appropriate. Withhold and then dose reduce VOTRIENT or permanently discontinue based on severity of hypertension. (2.2, 5.11)
- Risk of Impaired Wound Healing: Withhold VOTRIENT for at least 1 week prior to elective surgery. Do not administer for at least 2 weeks following major surgery and until adequate wound healing. The safety of resumption of VOTRIENT after resolution of wound healing complications has not been established. (5.12)
- Hypothyroidism: Monitor thyroid tests at baseline, during treatment and as clinically indicated and manage hypothyroidism as appropriate. (5.13)
- Proteinuria: Perform baseline and periodic urinalysis during treatment with follow up measurement of 24-hour urine protein as clinically indicated. Withhold VOTRIENT then resume at a reduced dose or permanently discontinue based on severity of proteinuria. Permanently discontinue in patients with nephrotic syndrome. (2.2, 5.14)
- Tumor Lysis Syndrome: Cases of tumor lysis syndrome (TLS) (some fatal) have been reported in patients with RCC and STS. Closely monitor patients at risk and treat as clinically indicated. (5.15)
- Infection: Serious infections (with or without neutropenia), some with fatal outcome, have been reported. Monitor for signs and symptoms of infection. Institute appropriate anti-infective therapy promptly. Consider interruption or discontinuation of VOTRIENT. (5.16)
- Embryo-Fetal Toxicity: Can cause fetal harm. Advise females of reproductive potential of the potential risk to the fetus and patients to use effective contraception. (5.19, 8.1, 8.3)

6 ADVERSE REACTIONS

- The most common adverse reactions in patients with RCC (≥ 20%) are diarrhea, hypertension, hair color changes (depigmentation), nausea, anorexia, and vomiting. (6.1)
- The most common adverse reactions in patients with STS (≥ 20%) are fatigue, diarrhea, nausea, decreased weight, hypertension, decreased appetite, vomiting, tumor pain, hair color changes, musculoskeletal pain, headache, dysgeusia, dyspnea, and skin hypopigmentation. (6.1)

To report SUSPECTED ADVERSE REACTIONS, contact Novartis Pharmaceuticals Corporation at 1-888-669-6682 or FDA at 1-800-FDA-1088 or www.fda.gov/medwatch.

7 DRUG INTERACTIONS

- Strong CYP3A4 Inhibitors: Avoid coadministration of VOTRIENT with strong CYP3A4 inhibitors. If coadministration cannot be avoided, reduce the dose of VOTRIENT. (2.4, 7.1)
- Strong CYP3A4 Inducers: Consider an alternate concomitant medication with no or minimal enzyme induction potential. VOTRIENT is not recommended if chronic use of strong CYP3A4 inducers cannot be avoided. (2.4, 7.1)
- CYP Substrates: Coadministration of VOTRIENT with agents with narrow therapeutic windows that are metabolized by CYP3A4, CYP2D6, or CYP2C8 is not recommended. (7.2)
- Concomitant Use With Simvastatin: Concomitant use of VOTRIENT with simvastatin increases the risk of alanine aminotransferase (ALT) elevations. Increase to weekly monitoring of liver function as recommended. Withhold VOTRIENT and resume at reduced dose, or permanently discontinue based on severity of hepatotoxicity. (7.3)
- Concomitant Use With Gastric Acid-Reducing Agents: Avoid concomitant use of VOTRIENT with gastric acid-reducing agents. Consider short-acting antacids in place of proton pump inhibitors (PPIs) and H2-receptor antagonists. Separate antacid and pazopanib dosing by several hours. (2.4, 7.4)

8 USE IN SPECIFIC POPULATIONS

- Lactation: Advise not to breastfeed. (8.2)

FULL PRESCRIBING INFORMATION

WARNING: HEPATOTOXICITY

Severe and fatal hepatotoxicity has been observed in clinical trials. Monitor hepatic function and interrupt, reduce, or discontinue dosing as recommended [see Warnings and Precautions (5.1)].

1 INDICATIONS AND USAGE

1.1 Renal Cell Carcinoma

VOTRIENT® is indicated for the treatment of adults with advanced renal cell carcinoma (RCC).

1.2 Soft Tissue Sarcoma

VOTRIENT is indicated for the treatment of adults with advanced soft tissue sarcoma (STS) who have received prior chemotherapy.

Limitations of Use: The efficacy of VOTRIENT for the treatment of patients with adipocytic STS or gastrointestinal stromal tumors has not been demonstrated.

2 DOSAGE AND ADMINISTRATION

2.1 Recommended Dosage

The recommended dosage of VOTRIENT is 800 mg (four 200 mg tablets) orally once daily without food (at least 1 hour before or 2 hours after a meal) until disease progression or unacceptable toxicity [see Clinical Pharmacology (12.3)]. The dosage should be modified for hepatic impairment and in patients taking certain concomitant drugs [see Dosage and Administration (2.3, 2.4)].

Swallow tablets whole. Do not crush tablets due to the potential for increased rate of absorption, which may affect systemic exposure [see Clinical Pharmacology (12.3)].

If a dose is missed, it should not be taken if it is < 12 hours until the next dose.

2.2 Dosage Modifications for Adverse Reactions

Table 1 summarizes the recommended dose reductions.

Table 1. Recommended Dose Reductions of VOTRIENT for Adverse Reactions
Dose reduction | For renal cell carcinoma | For soft tissue sarcoma
First | 400 mg orally once daily | 600 mg orally once daily
Second | 200 mg orally once daily | 400 mg orally once daily

Permanently discontinue VOTRIENT in patients unable to tolerate the second dose reduction.

Table 2 summarizes the recommended dosage modifications for adverse reactions.

Table 2. Recommended Dosage Modifications of VOTRIENT for Adverse Reactions
Adverse reaction | Severitya | Dosage modification
Hepatic Toxicity [see Warnings and Precautions (5.1)] | Isolated ALT elevations between 3 × ULN and 8 × ULN | Continue and monitor liver function weekly until ALT returns to Grade 1 or baseline.
 | Isolated ALT elevations of > 8 × ULN | Withhold until improvement to Grade 1 or baseline. If the potential benefit for resuming treatment with VOTRIENT is considered to outweigh the risk for hepatotoxicity, then resume at a reduced dose of no more than 400 mg once daily and measure serum liver tests weekly for 8 weeks. Permanently discontinue if ALT elevations > 3 × ULN recur despite dose reduction(s).
 | ALT elevations > 3 × ULN occur concurrently with bilirubin elevations > 2 × ULN | Permanently discontinue and continue to monitor until resolution. Patients with only a mild, indirect (unconjugated) hyperbilirubinemia, known as Gilbert’s syndrome, and ALT elevations > 3 × ULN should be managed per the recommendations outlined for isolated ALT elevations.
Left Ventricular Systolic Dysfunction [see Warnings and Precautions (5.3)] | Symptomatic or Grade 3 | Withhold until improvement to Grade < 3. Resume treatment based on medical judgement.
 | Grade 4 | Permanently discontinue.
Hemorrhagic Events [see Warnings and Precautions (5.4)] | Grade 2 | Withhold until improvement to Grade ≤ 1. Resume at reduced dose (see Table 1). Permanently discontinue if Grade 2 recurs after dose interruption and reduction.
 | Grade 3 or 4 | Permanently discontinue.
Arterial Thromboembolic Events [see Warnings and Precautions (5.5)] | Any grade | Permanently discontinue.
Venous Thromboembolic Events [see Warnings and Precautions (5.6)] | Grade 3 | Withhold VOTRIENT and resume at same dose if managed with appropriate therapy for at least one week.
 | Grade 4 | Permanently discontinue.
Thrombotic Microangiopathy [see Warnings and Precautions (5.7)] | Any grade | Permanently discontinue.
Gastrointestinal Perforation [see Warnings and Precautions (5.8)] | Any grade | Permanently discontinue.
Gastrointestinal Fistula [see Warnings and Precautions (5.8)] | Grade 2 or 3 | Withhold and resume based on medical judgement.
 | Grade 4 | Permanently discontinue.
Interstitial Lung Disease / Pneumonitis [see Warnings and Precautions (5.9)] | Any grade | Permanently discontinue.
Posterior Reversible Encephalopathy Syndrome [see Warnings and Precautions (5.10)] | Any grade | Permanently discontinue.
Hypertension [see Warnings and Precautions (5.11)] | Grade 2 or 3 | Reduce dose (see Table 1) and initiate or adjust anti-hypertensive therapy. Permanently discontinue if hypertension remains Grade 3 despite dose reduction(s) and adjustment of anti-hypertensive therapy.
 | Grade 4 or hypertensive crisis | Permanently discontinue.
Proteinuria [see Warnings and Precautions (5.14)] | 24-hour urine protein ≥ 3 grams | Withhold until improvement to Grade ≤ 1. Resume at a reduced dose (see Table 1). Permanently discontinue if 24-hour urine protein ≥ 3 grams does not improve or recurs despite dose reductions.
 | Confirmed nephrotic syndrome | Permanently discontinue.
Abbreviations: ALT, alanine aminotransferase; ULN, upper limit of normal.
aNational Cancer Institute Common Terminology Criteria for Adverse Events, version 5.

2.3 Dosage Modifications for Hepatic Impairment

Moderate and Severe Hepatic Impairment

In patients with moderate hepatic impairment [total bilirubin > 1.5 to 3 × upper limit of normal (ULN) and any alanine aminotransferase (ALT) value], consider alternatives to VOTRIENT. If VOTRIENT is used in patients with moderate hepatic impairment, reduce the VOTRIENT dose to 200 mg orally once daily.

VOTRIENT is not recommended in patients with severe hepatic impairment (total bilirubin > 3 × ULN and any ALT value) [see Use in Specific Populations (8.7)].

2.4 Dosage Modifications for Drug Interactions

Strong CYP3A4 Inhibitors

Avoid concomitant use of strong CYP3A4 inhibitors by use of an alternate concomitant medication with no or minimal potential to inhibit CYP3A4. If coadministration of a strong CYP3A4 inhibitor is warranted, reduce the dose of VOTRIENT to 400 mg [see Drug Interactions (7.1)].

Strong CYP3A4 Inducers

Avoid concomitant use of strong CYP3A4 inducers by use of an alternate concomitant medication with no or minimal enzyme induction potential. VOTRIENT is not recommended in patients who cannot avoid chronic use of strong CYP3A4 inducers [see Drug Interactions (7.1)].

Gastric Acid-Reducing Agents

Avoid concomitant use of gastric acid-reducing agents. If concomitant use of a gastric acid-reducing agent cannot be avoided, consider short-acting antacid in place of proton pump inhibitors (PPIs) and H2-receptor antagonists. Separate short-acting antacid and VOTRIENT dosing by several hours [see Drug Interactions (7.4), Clinical Pharmacology (12.3)].

3 DOSAGE FORMS AND STRENGTHS

Tablets: 200 mg, modified capsule-shaped, gray or pink, film-coated with ‘GS JT’ debossed on one side.

4 CONTRAINDICATIONS

None.

5 WARNINGS AND PRECAUTIONS

5.1 Hepatic Toxicity

Hepatotoxicity, manifested as increases in ALT, aspartate aminotransferase (AST) and bilirubin, occurred in patients who received VOTRIENT. This hepatotoxicity can be severe and fatal. Patients older than 65 years are at greater risk for hepatotoxicity [see Use in Specific Populations (8.5)]. Transaminase elevations occur early in the course of treatment; 92% of all transaminase elevations of any grade occurred in the first 18 weeks.

In the randomized RCC trial (VEG105192), ALT > 3 × ULN occurred in 18% and ALT > 10 × ULN occurred in 4% of the 290 patients who received VOTRIENT. Concurrent elevation in ALT > 3 × ULN and bilirubin > 2 × ULN in the absence of significant alkaline phosphatase > 3 × ULN occurred in 2%. In the monotherapy trials, 2 patients died with disease progression and hepatic failure.

In the randomized STS trial (VEG110727), ALT > 3 × ULN occurred in 18% and ALT > 8 × ULN occurred in 5% of the 240 patients who received VOTRIENT. Concurrent elevation in ALT > 3 × ULN and bilirubin > 2 × ULN in the absence of significant alkaline phosphatase > 3 × ULN occurred in 2%. One patient died of hepatic failure.

Monitor liver tests at baseline; at Weeks 3, 5, 7, and 9; at Month 3 and Month 4; and then periodically as clinically indicated. Increase to weekly monitoring for patients with elevated ALT until ALT returns to Grade 1 or baseline. Withhold VOTRIENT and resume at reduced dose with continued weekly monitoring for 8 weeks, or permanently discontinue with weekly monitoring until resolution based on severity of hepatotoxicity [see Dosage and Administration (2.2)].

Gilbert’s Syndrome

VOTRIENT is a uridine diphosphate (UDP)-glucuronosyl transferase 1A1 (UGT1A1) inhibitor. Mild, indirect (unconjugated) hyperbilirubinemia may occur in patients with Gilbert’s syndrome [see Clinical Pharmacology (12.5)]. In patients with only a mild indirect hyperbilirubinemia known as Gilbert’s syndrome, manage elevation in ALT > 3 × ULN per the recommendations outlined for isolated ALT elevations [see Dosage and Administration (2.2)].

Concomitant Use of Simvastatin

Concomitant use of VOTRIENT and simvastatin increases the risk of ALT elevations [see Drug Interactions (7.3)]. Insufficient data are available to assess the risk of concomitant administration of alternative statins and VOTRIENT.

5.2 QT Prolongation and Torsades de Pointes

In the RCC trials, 558/586 patients were subject to routine electrocardiogram (ECG) monitoring and QT prolongation ≥ 500 msec was identified in 2% of these 558 patients. In monotherapy trials, torsades de pointes occurred in < 1% of 977 patients who received VOTRIENT.

In the randomized RCC (VEG105192) and STS (VEG110727) trials, 1% (3/290) and 0.4% (1/240) of patients, respectively, who received VOTRIENT had post-baseline values between 500 to 549 msec. Post-baseline QT data were only collected in the STS trial if ECG abnormalities were reported as an adverse reaction.

Monitor patients who are at significant risk of developing QTc prolongation, including patients with a history of QT interval prolongation, in patients taking antiarrhythmics or other medications that may prolong QT interval, and those with relevant preexisting cardiac disease [see Drug Interactions (7.5)]. Monitor ECG and electrolytes (e.g., calcium, magnesium, potassium) at baseline and as clinically indicated. Correct hypokalemia, hypomagnesemia, and hypocalcemia prior to initiating VOTRIENT and during treatment.

5.3 Cardiac Dysfunction

Cardiac dysfunction, including decreased left ventricular ejection fraction (LVEF) and congestive heart failure, occurred in patients who received VOTRIENT.

In the RCC trials, cardiac dysfunction was observed in 0.6% of 586 patients without routine on-study LVEF monitoring. In the randomized RCC trial (VEG105192), myocardial dysfunction was defined as symptoms of cardiac dysfunction or ≥ 15% absolute decline in LVEF compared with baseline or a decline in LVEF of ≥ 10% compared with baseline that is also below the lower limit of normal. In an RCC trial (COMPARZ), myocardial dysfunction occurred in 13% of the 362 patients on VOTRIENT who had a baseline and post-baseline LVEF measurements. Congestive heart failure occurred in 0.5% of patients.

In the randomized STS trial (VEG110727), myocardial dysfunction occurred in 11% of the 142 patients who had a baseline and a post-baseline LVEF measurements. One percent (3/240) of patients who received VOTRIENT had congestive heart failure, which did not resolve in one patient. Fourteen of the 16 patients with myocardial dysfunction treated with VOTRIENT had concurrent hypertension which may have exacerbated cardiac dysfunction in patients at risk (e.g., those with prior anthracycline therapy) possibly by increasing cardiac afterload.

Monitor blood pressure and manage as appropriate [see Warnings and Precautions (5.11)]. Monitor for clinical signs or symptoms of congestive heart failure. Conduct baseline and periodic evaluation of LVEF in patients at risk of cardiac dysfunction, including previous anthracycline exposure. Withhold or permanently discontinue VOTRIENT based on severity of cardiac dysfunction [see Dosage and Administration (2.2)].

5.4 Hemorrhagic Events

In the RCC trials, fatal hemorrhage occurred in 0.9% of 586 patients, and cerebral/intracranial hemorrhage was observed in < 1% (2/586) of patients treated with VOTRIENT.

In the randomized RCC trial (VEG105192), 13% of 290 patients treated with VOTRIENT experienced at least 1 hemorrhagic event. The most common hemorrhagic events were hematuria (4%), epistaxis (2%), hemoptysis (2%), and rectal hemorrhage (1%). Nine of 37 patients treated with VOTRIENT who had hemorrhagic events experienced serious events, including pulmonary, gastrointestinal, and genitourinary hemorrhage. One percent of patients treated with VOTRIENT died from hemorrhage.

In the randomized STS trial (VEG110727), 22% of 240 patients treated with VOTRIENT experienced at least 1 hemorrhagic event. The most common hemorrhagic events were epistaxis (8%), mouth hemorrhage (3%), and anal hemorrhage (2%). Grade 4 hemorrhagic events occurred in 1% of patients and included intracranial hemorrhage, subarachnoid hemorrhage, and peritoneal hemorrhage.

VOTRIENT has not been studied in patients who have a history of hemoptysis, cerebral hemorrhage, or clinically significant gastrointestinal hemorrhage in the past 6 months. Withhold VOTRIENT and resume at reduced dose or permanently discontinue based on severity of hemorrhagic events [see Dosage and Administration (2.2)].

5.5 Arterial Thromboembolic Events

In the RCC trials, fatal arterial thromboembolic events occurred in 0.3% of 586 patients. In the randomized RCC trial (VEG105192), 2% of 290 patients who received VOTRIENT experienced myocardial infarction or ischemia, 0.3% had a cerebrovascular accident, and 1% had an event of transient ischemic attack.

In the randomized STS trial (VEG110727), 2% of 240 patients who received VOTRIENT experienced a myocardial infarction or ischemia and 0.4% had a cerebrovascular accident.

VOTRIENT has not been studied in patients who have had an arterial thromboembolic event within the previous 6 months. Permanently discontinue VOTRIENT in case of an arterial thromboembolic event [see Dosage and Administration (2.2)].

5.6 Venous Thromboembolic Events

Venous thromboembolic events (VTEs), including venous thrombosis and fatal pulmonary embolus (PE), occurred in patients who received VOTRIENT.

In the randomized RCC trial (VEG105192), VTEs occurred in 1% of 290 patients who received VOTRIENT. In the randomized STS trial (VEG110727), VTEs were reported in 5% of 240 patients who received VOTRIENT. Fatal PE occurred in 1% (2/240).

Monitor for signs and symptoms of VTE and PE. Withhold VOTRIENT and then resume at same dose or permanently discontinue based on severity of VTE [see Dosage and Administration (2.2)].

5.7 Thrombotic Microangiopathy

Thrombotic microangiopathy (TMA), including thrombotic thrombocytopenic purpura (TTP) and hemolytic uremic syndrome (HUS), occurred in clinical trials of VOTRIENT as monotherapy, in combination with bevacizumab, and in combination with topotecan. VOTRIENT is not indicated for use in combination with other agents. Six of the 7 TMA cases occurred within 90 days of the initiation of VOTRIENT. Improvement of TMA was observed after treatment was discontinued.

Monitor for signs and symptoms of TMA. Permanently discontinue VOTRIENT in patients developing TMA. Manage as clinically indicated.

5.8 Gastrointestinal Perforation and Fistula

In the RCC and STS trials, gastrointestinal perforation or fistula occurred in 0.9% of 586 patients and 1% of 382 patients who received VOTRIENT, respectively. Fatal perforations occurred in 0.3% (2/586) of these patients in the RCC trials and in 0.3% (1/382) of these patients in the STS trials.

Monitor for signs and symptoms of gastrointestinal perforation or fistula. Withhold VOTRIENT in case of Grade 2 or 3 gastrointestinal fistula and resume based on medical judgement. Permanently discontinue VOTRIENT in case of gastrointestinal perforation or Grade 4 gastrointestinal fistula [see Dosage and Administration (2.2)].

5.9 Interstitial Lung Disease/Pneumonitis

Interstitial lung disease (ILD)/pneumonitis, which can be fatal, has been reported with VOTRIENT across clinical trials. ILD/pneumonitis occurred in 0.1% of patients treated with VOTRIENT.

Monitor patients for pulmonary symptoms indicative of ILD/pneumonitis. Permanently discontinue VOTRIENT in patients who develop ILD or pneumonitis [see Dosage and Administration (2.2)].

5.10 Posterior Reversible Encephalopathy Syndrome

Posterior Reversible Encephalopathy Syndrome (PRES) has been reported in patients who received VOTRIENT and may be fatal. PRES is a neurological disorder which can present with headache, seizure, lethargy, confusion, blindness, and other visual and neurologic disturbances. Mild to severe hypertension may be present. Confirm diagnosis of PRES by magnetic resonance imaging.

Permanently discontinue VOTRIENT in patients who develop PRES.

5.11 Hypertension

Hypertension (systolic blood pressure ≥ 150 mmHg or diastolic blood pressure ≥ 100 mmHg) and hypertensive crisis were observed in patients treated with VOTRIENT.

Approximately 40% of patients who received VOTRIENT experienced hypertension, with Grade 3 occurring in 4% to 7% of patients [see Adverse Reactions (6.1)]. About 40% of cases occurred by Day 9 and about 90% of cases occurred in the first 18 weeks across clinical trials. Approximately 1% of patients required permanent discontinuation of VOTRIENT because of hypertension.

Do not initiate VOTRIENT in patients with uncontrolled hypertension. Optimize blood pressure prior to initiating VOTRIENT. Monitor blood pressure as clinically indicated and initiate and adjust antihypertensive therapy as appropriate. Withhold and then dose reduce VOTRIENT or permanently discontinue based on severity of hypertension [see Dosage and Administration (2.2)].

5.12 Risk of Impaired Wound Healing

Impaired wound healing complications can occur in patients who receive drugs that inhibit the vascular endothelial growth factor (VEGF) signaling pathway. Therefore, VOTRIENT has the potential to adversely affect wound healing.

Withhold VOTRIENT at least 1 week prior to elective surgery. Do not administer for at least 2 weeks following major surgery and until adequate wound healing. The safety of resumption of VOTRIENT after resolution of wound healing complications has not been established.

5.13 Hypothyroidism

Hypothyroidism, confirmed based on a simultaneous rise of TSH and decline of T4, occurred in 7% of 290 patients who received VOTRIENT in the randomized RCC trial (VEG105192) and in 5% of 240 patients who received VOTRIENT in the randomized STS trial (VEG110727). Hypothyroidism occurred in 4% of the 586 patients in the RCC trials and 5% of the 382 patients in the STS trials.

Monitor thyroid tests at baseline, during treatment and as clinically indicated and manage hypothyroidism as appropriate.

5.14 Proteinuria

In the randomized RCC trial (VEG105192), proteinuria occurred in 9% of 290 patients who received VOTRIENT. In 2 patients, proteinuria led to discontinuation of VOTRIENT.

In the randomized STS trial (VEG110727), proteinuria occurred in 1% of 240 patients and nephrotic syndrome occurred in 1 patient. Treatment was discontinued in the patient with nephrotic syndrome.

Perform baseline and periodic urinalysis during treatment with follow up measurement of 24-hour urine protein as clinically indicated. Withhold VOTRIENT then resume at a reduced dose or permanently discontinue based on severity of proteinuria. Permanently discontinue in patients with nephrotic syndrome [see Dosage and Administration (2.2)].

5.15 Tumor Lysis Syndrome

Cases of tumor lysis syndrome (TLS), including fatal cases, have been reported in RCC and STS patients treated with VOTRIENT [see Adverse Reactions (6.2)]. Patients may be at risk of TLS if they have rapidly growing tumors, a high tumor burden, renal dysfunction, or dehydration. Closely monitor patients at risk, consider appropriate prophylaxis, and treat as clinically indicated.

5.16 Infection

Serious infections (with or without neutropenia), including some with fatal outcome, have been reported. Monitor patients for signs and symptoms of infection. Institute appropriate anti-infective therapy promptly and consider interruption or discontinuation of VOTRIENT for serious infections.

5.17 Increased Toxicity With Other Cancer Therapy

VOTRIENT is not indicated for use in combination with other agents. Clinical trials of VOTRIENT in combination with pemetrexed and lapatinib were terminated early due to increased toxicity and mortality. The fatal toxicities observed included pulmonary hemorrhage, gastrointestinal hemorrhage, and sudden death. A safe and effective combination dose has not been established with these regimens.

5.18 Increased Toxicity in Developing Organs

The safety and effectiveness of VOTRIENT in pediatric patients have not been established. VOTRIENT is not indicated for use in pediatric patients. Based on its mechanism of action, pazopanib may have severe effects on organ growth and maturation in patients younger than 2 years of age [see Use in Specific Populations (8.4)].

5.19 Embryo-Fetal Toxicity

Based on findings from animal studies and its mechanism of action, VOTRIENT can cause fetal harm when administered to a pregnant woman. Administration of VOTRIENT to pregnant rats and rabbits during the period of organogenesis resulted in maternal toxicity, teratogenicity, and abortion at systemic exposures lower than that observed at the maximum recommended human dose (MRHD) of 800 mg (based on area under the curve [AUC]).

Advise pregnant women of the potential risk to a fetus. Advise females of reproductive potential to use effective contraception during treatment with VOTRIENT and for at least 2 weeks following the final dose. Advise males (including those who have had vasectomies) with female partners of reproductive potential to use condoms during treatment with VOTRIENT and for at least 2 weeks after the last dose [see Use in Specific Populations (8.1, 8.3)].

6 ADVERSE REACTIONS

The following clinically significant adverse reactions are elsewhere in the labeling:

- Hepatic Toxicity [see Warnings and Precautions (5.1)]
- QT Prolongation and Torsades de Pointes [see Warnings and Precautions (5.2)]
- Cardiac Dysfunction [see Warnings and Precautions (5.3)]
- Hemorrhagic Events [see Warnings and Precautions (5.4)]
- Arterial Thromboembolic Events [see Warnings and Precautions (5.5)]
- Venous Thromboembolic Events [see Warnings and Precautions (5.6)]
- Thrombotic Microangiopathy (TMA) [see Warnings and Precautions (5.7)]
- Gastrointestinal Perforation and Fistula [see Warnings and Precautions (5.8)]
- Interstitial Lung Disease (ILD)/Pneumonitis [see Warnings and Precautions (5.9)]
- Posterior Reversible Encephalopathy Syndrome (PRES) [see Warnings and Precautions (5.10)]
- Hypertension [see Warnings and Precautions (5.11)]
- Hypothyroidism [see Warnings and Precautions (5.13)]
- Proteinuria [see Warnings and Precautions (5.14)]
- Tumor Lysis Syndrome [see Warnings and Precautions (5.15)]
- Infection [see Warnings and Precautions (5.16)]

6.1 Clinical Trials Experience

Because clinical trials are conducted under widely varying conditions, adverse reaction rates observed in the clinical trials of a drug cannot be directly compared with rates in the clinical trials of another drug and may not reflect the rates observed in practice.

The data described in the WARNINGS AND PRECAUTIONS section reflect exposure of 977 patients who received VOTRIENT as a single agent, including 586 VOTRIENT-treated patients with RCC. With a median duration of treatment of 7.4 months (range, 0.1 to 27.6) in these 977 patients, the most common adverse reactions (≥ 20%) in these 586 patients were diarrhea, hypertension, hair color change, nausea, fatigue, anorexia, and vomiting.

The data described in the WARNINGS AND PRECAUTIONS also reflects exposure of 382 patients with advanced soft tissue sarcoma who received VOTRIENT as a single agent, with a median duration of treatment of 3.6 months (range, 0 to 53). The most common adverse reactions (≥ 20%) in these 382 patients were fatigue, diarrhea, nausea, decreased weight, hypertension, decreased appetite, vomiting, tumor pain, hair color changes, musculoskeletal pain, headache, dysgeusia, dyspnea, and skin hypopigmentation.

Renal Cell Carcinoma

The safety of VOTRIENT was evaluated in 290 patients with RCC who participated in VEG105192, a randomized, double-blind, placebo-controlled trial [see Clinical Studies (14.1)]. The median duration of treatment was 7.4 months (range, 0 to 23) for patients who received VOTRIENT.

Forty-two percent of patients on VOTRIENT required a dose interruption and 36% required a dose reduction.

Table 3 presents adverse reactions in VEG105192.

Table 3. Adverse Reactions (≥ 10%) in Patients with RCC Who Received VOTRIENT in VEG105192
 | VOTRIENT (N = 290) |  |  | Placebo (N = 145)
 | All Gradesa | Grade 3 | Grade 4 | All Gradesa | Grade 3 | Grade 4
Adverse reactions | % | % | % | % | % | %
Diarrhea | 52 | 3 | < 1 | 9 | < 1 | 0
Hypertension | 40 | 4 | 0 | 10 | < 1 | 0
Hair color changes | 38 | < 1 | 0 | 3 | 0 | 0
Nausea | 26 | < 1 | 0 | 9 | 0 | 0
Anorexia | 22 | 2 | 0 | 10 | < 1 | 0
Vomiting | 21 | 2 | < 1 | 8 | 2 | 0
Fatigue | 19 | 2 | 0 | 8 | 1 | 1
Asthenia | 14 | 3 | 0 | 8 | 0 | 0
Abdominal pain | 11 | 2 | 0 | 1 | 0 | 0
Headache | 10 | 0 | 0 | 5 | 0 | 0
Abbreviation: RCC, renal cell carcinoma.
aNational Cancer Institute Common Terminology Criteria for Adverse Events, version 3.

Other adverse reactions observed more commonly in patients treated with VOTRIENT than placebo and that occurred in < 10% (any grade) were alopecia (8% versus < 1%), chest pain (5% versus 1%), dysgeusia (8% versus < 1%), dyspepsia (5% versus < 1%), dysphonia (4% versus < 1%), facial edema (1% versus 0%), palmar-plantar erythrodysesthesia (6% versus < 1%), proteinuria (9% versus 0%), rash (8% versus 3%), skin depigmentation (3% versus 0%), and weight decreased (9% versus 3%).

Table 4 presents the laboratory abnormalities in VEG105192.

Table 4. Select Laboratory Abnormalities (> 10%) in Patients with RCC Who Received VOTRIENT with a Difference Between Arms of ≥ 5% Compared to Placebo in VEG105192
 | VOTRIENT (N = 290) |  |  | Placebo (N = 145)
 | All Gradesa | Grade 3 | Grade 4 | All Gradesa | Grade 3 | Grade 4
Parameters | % | % | % | % | % | %
Chemistry
ALT increased | 53 | 10 | 2 | 22 | 1 | 0
AST increased | 53 | 7 | < 1 | 19 | < 1 | 0
Glucose increased | 41 | < 1 | 0 | 33 | 1 | 0
Total bilirubin increased | 36 | 3 | < 1 | 10 | 1 | < 1
Phosphorus decreased | 34 | 4 | 0 | 11 | 0 | 0
Sodium decreased | 31 | 4 | 1 | 24 | 4 | 0
Magnesium decreased | 26 | < 1 | 1 | 14 | 0 | 0
Glucose decreased | 17 | 0 | < 1 | 3 | 0 | 0
Hematologic
Leukopenia | 37 | 0 | 0 | 6 | 0 | 0
Neutropenia | 34 | 1 | < 1 | 6 | 0 | 0
Thrombocytopenia | 32 | < 1 | < 1 | 5 | 0 | < 1
Lymphocytopenia | 31 | 4 | < 1 | 24 | 1 | 0
Abbreviations: ALT, alanine aminotransferase; AST, aspartate aminotransferase; RCC, renal cell carcinoma.
aNational Cancer Institute Common Terminology Criteria for Adverse Events, version 3.

Additional adverse reactions from other clinical trials in patients with RCC who received VOTRIENT include arthralgia and muscle spasms.

Soft Tissue Sarcoma

The safety of VOTRIENT was evaluated in 240 patients who participated in VEG110727, a randomized, double-blind, placebo-controlled trial [see Clinical Studies (14.2)]. The median duration of treatment was 4.5 months (range, 0 to 24) for patients who received VOTRIENT.

Fifty-eight percent of patients on VOTRIENT required a dose interruption and 38% required a dose reduction. Seventeen percent of patients who received VOTRIENT discontinued therapy due to adverse reactions.

Table 5 presents the adverse reactions in VEG110727.

Table 5. Adverse Reactions (≥ 10%) in Patients with STS Who Received VOTRIENT in VEG110727
 | VOTRIENT (N = 240) |  |  | Placebo (N = 123)
 | All Gradesa | Grade 3 | Grade 4 | All Gradesa | Grade 3 | Grade 4
Adverse reactions | % | % | % | % | % | %
Fatigue | 65 | 13 | 1 | 48 | 4 | 1
Diarrhea | 59 | 5 | 0 | 15 | 1 | 0
Nausea | 56 | 3 | 0 | 22 | 2 | 0
Weight decreased | 48 | 4 | 0 | 15 | 0 | 0
Hypertension | 42 | 7 | 0 | 6 | 0 | 0
Appetite decreased | 40 | 6 | 0 | 19 | 0 | 0
Hair color changes | 39 | 0 | 0 | 2 | 0 | 0
Vomiting | 33 | 3 | 0 | 11 | 1 | 0
Tumor pain | 29 | 8 | 0 | 21 | 7 | 2
Dysgeusia | 28 | 0 | 0 | 3 | 0 | 0
Headache | 23 | 1 | 0 | 8 | 0 | 0
Musculoskeletal pain | 23 | 2 | 0 | 20 | 2 | 0
Myalgia | 23 | 2 | 0 | 9 | 0 | 0
Gastrointestinal pain | 23 | 3 | 0 | 9 | 4 | 0
Dyspnea | 20 | 5 | < 1 | 17 | 5 | 1
Exfoliative rash | 18 | < 1 | 0 | 9 | 0 | 0
Cough | 17 | < 1 | 0 | 12 | < 1 | 0
Peripheral edema | 14 | 2 | 0 | 9 | 2 | 0
Mucositis | 12 | 2 | 0 | 2 | 0 | 0
Alopecia | 12 | 0 | 0 | 1 | 0 | 0
Dizziness | 11 | 1 | 0 | 4 | 0 | 0
Skin disorderb | 11 | 2 | 0 | 1 | 0 | 0
Skin hypopigmentation | 11 | 0 | 0 | 0 | 0 | 0
Stomatitis | 11 | < 1 | 0 | 3 | 0 | 0
Chest pain | 10 | 2 | 0 | 6 | 0 | 0
Abbreviation: STS, soft tissue sarcoma.
aNational Cancer Institute Common Terminology Criteria for Adverse Events, version 3.
b27 of the 28 cases of skin disorder were palmar-plantar erythrodysesthesia.

Other adverse reactions observed more commonly in patients treated with VOTRIENT that occurred in ≥ 5% of patients and at an incidence of more than 2% difference from placebo included insomnia (9% versus 6%), hypothyroidism (8% versus 0%), dysphonia (8% versus 2%), epistaxis (8% versus 2%), left ventricular dysfunction (8% versus 4%), dyspepsia (7% versus 2%), dry skin (6% versus < 1%), chills (5% versus 1%), vision blurred (5% versus 2%), and nail disorder (5% versus 0%).

Table 6 presents the laboratory abnormalities in VEG110727.

Table 6. Select Laboratory Abnormalities (> 10%) in Patients with STS Who Received VOTRIENT with a Difference Between Arms of ≥ 5% Compared to Placebo in VEG110727
 | VOTRIENT (N = 240) |  |  | Placebo (N = 123)
 | All Gradesa | Grade 3 | Grade 4 | All Gradesa | Grade 3 | Grade 4
Parameters | % | % | % | % | % | %
Chemistry
AST increased | 51 | 5 | 3 | 22 | 2 | 0
ALT increased | 46 | 8 | 2 | 18 | 2 | 1
Glucose increased | 45 | < 1 | 0 | 35 | 2 | 0
Albumin decreased | 34 | 1 | 0 | 21 | 0 | 0
Alkaline phosphatase increased | 32 | 3 | 0 | 23 | 1 | 0
Sodium decreased | 31 | 4 | 0 | 20 | 3 | 0
Total bilirubin increased | 29 | 1 | 0 | 7 | 2 | 0
Potassium increased | 16 | 1 | 0 | 11 | 0 | 0
Hematologic
Leukopenia | 44 | 1 | 0 | 15 | 0 | 0
Lymphocytopenia | 43 | 10 | 0 | 36 | 9 | 2
Thrombocytopenia | 36 | 3 | 1 | 6 | 0 | 0
Neutropenia | 33 | 4 | 0 | 7 | 0 | 0
Abbreviations: ALT, alanine aminotransferase; AST, aspartate aminotransferase; STS, soft tissue sarcoma.
aNational Cancer Institute Common Terminology Criteria for Adverse Events, version 3.

Other Clinically Relevant Adverse Reactions

Lipase Elevations

In a single-arm RCC trial (VEG102616), elevated lipase was observed for 27% of 181 patients with available laboratory data. Elevated lipase as an adverse reaction was reported for 4% of 225 patients, including 2.7% (6/225) with Grade 3 and 0.4% (1/225) with Grade 4. In the RCC trials, clinical pancreatitis was observed in < 1% of 586 patients.

Pneumothorax

Two of 290 patients (0.7%) treated with VOTRIENT in the randomized RCC trial (VEG105192) and 8 of 240 patients (3.3%) treated with VOTRIENT in the randomized STS trial (VEG110727) developed a pneumothorax.

Bradycardia

In the randomized RCC trial (VEG105192), bradycardia based on vital signs (< 60 beats per minute) was observed in 19% of 280 patients treated with VOTRIENT. Bradycardia was reported as an adverse reaction in 2% of 290 patients.

In the randomized STS trial (VEG110727), bradycardia based on vital signs (< 60 beats per minute) was observed in 19% of 238 patients treated with VOTRIENT. Bradycardia was reported as an adverse reaction in 2% of 240 patients.

Adverse Reactions in East Asian Patients

In an analysis of pooled clinical trial data (N = 1938) with VOTRIENT, Grade 3 and Grade 4 neutropenia (12% versus 2%), thrombocytopenia (6% versus < 1%) and palmar-plantar erythrodysesthesia (6% versus 2%) were observed more frequently in patients of East Asian descent than in patients of non-East Asian descent.

6.2 Postmarketing Experience

The following adverse reactions have been identified during post-approval use of VOTRIENT. Because these reactions are reported voluntarily from a population of uncertain size, it is not always possible to reliably estimate the frequency or establish a causal relationship to drug exposure.

Blood and Lymphatic System Disorders: Polycythemia

Eye Disorders: Retinal detachment/tear

Gastrointestinal Disorders: Pancreatitis

Metabolic and Nutrition Disorder: Tumor lysis syndrome (including fatal cases)

Vascular Disorders: Arterial (including aortic) aneurysms, dissections, and rupture (including fatal cases)

7 DRUG INTERACTIONS

7.1 Effect of Other Drugs on VOTRIENT

Strong CYP3A4 Inhibitors

Coadministration of pazopanib with strong inhibitors of CYP3A4 increases pazopanib concentrations [see Clinical Pharmacology (12.3)]. Avoid coadministration of VOTRIENT with strong CYP3A4 inhibitors and consider an alternate concomitant medication with no or minimal enzyme inhibition potential. If coadministration of a strong CYP3A4 inhibitor cannot be avoided, reduce the dose of VOTRIENT [see Dosage and Administration (2.4)].

Strong CYP3A4 Inducers

Coadministration of strong CYP3A4 inducers may decrease plasma pazopanib concentrations. Consider an alternate concomitant medication with no or minimal enzyme induction potential. VOTRIENT is not recommended if chronic use of strong CYP3A4 inducers cannot be avoided [see Dosage and Administration (2.4)].

Transporters

Coadministration of strong inhibitors of P-gp or BCRP may increase pazopanib concentrations. Avoid concomitant use of VOTRIENT with strong inhibitors of P-gp or BCRP. Consider selection of alternative concomitant medicinal products with no or minimal potential to inhibit P-gp or BCRP.

7.2 Effects of VOTRIENT on Other Drugs

CYP Substrates

Coadministration of VOTRIENT with agents with narrow therapeutic windows that are metabolized by CYP3A4, CYP2D6, or CYP2C8 may result in inhibition of the metabolism of these products and create the potential for serious adverse reactions. The concomitant use of VOTRIENT with agents with narrow therapeutic windows that are metabolized by CYP3A4, CYP2D6, or CYP2C8 is not recommended [see Clinical Pharmacology (12.3)].

7.3 Concomitant Use With Simvastatin

Concomitant use of VOTRIENT with simvastatin increases the incidence of ALT elevations. Across clinical trials of VOTRIENT as a single agent, ALT > 3 × ULN was reported in 126/895 (14%) of patients who did not use statins compared with 11/41 (27%) of patients who had concomitant use of simvastatin. If a patient receiving concomitant simvastatin develops ALT elevations, increase to weekly monitoring of liver function as recommended. Withhold VOTRIENT and resume at reduced dose, or permanently discontinue based on severity of hepatotoxicity [see Dosage and Administration (2.2), Warnings and Precautions (5.1)]. Insufficient data are available to assess the risk of concomitant administration of alternative statins and VOTRIENT.

7.4 Concomitant Use With Gastric Acid-Reducing Agents

Concomitant use of VOTRIENT with esomeprazole, a PPI, decreased the exposure of pazopanib. Avoid concomitant use of VOTRIENT with gastric acid-reducing agents. If concomitant administration with a gastric acid-reducing agent cannot be avoided, consider short-acting antacids in place of PPIs and H2-receptor antagonists. Separate short-acting antacid and pazopanib dosing by several hours to avoid a reduction in pazopanib exposure [see Dosage and Administration (2.4), Clinical Pharmacology (12.3)].

7.5 Drugs That Prolong the QT Interval

VOTRIENT is associated with QTc interval prolongation [see Warnings and Precautions (5.2), Clinical Pharmacology (12.2)]. Avoid coadministration of VOTRIENT with drugs known to prolong the QT/QTc interval.

8 USE IN SPECIFIC POPULATIONS

8.1 Pregnancy

Risk Summary

Based on animal reproduction studies and its mechanism of action [see Clinical Pharmacology (12.1)], VOTRIENT can cause fetal harm when administered to a pregnant woman. There are no available data on VOTRIENT use in pregnant women to evaluate for a drug-associated risk. In animal developmental and reproductive toxicology studies, oral administration of pazopanib to pregnant rats and rabbits throughout organogenesis resulted in teratogenicity, and abortion at systemic exposures lower than that observed at the MRHD of 800 mg/day (based on AUC) (see Data). Advise pregnant women of the potential risk to a fetus.

The estimated background risk of major birth defects and miscarriage for the indicated population is unknown. All pregnancies have a background risk of birth defect, loss or other adverse outcomes. In the U.S. general population, the estimated background risk of major birth defects in clinically recognized pregnancies and miscarriage is 2% to 4% and 15% to 20%, respectively.

Data

Animal Data

In a female fertility and early embryonic development study, female rats were administered oral pazopanib at least 15 days prior to mating and for 6 days after mating, which resulted in increased pre-implantation loss and early resorptions at dosages greater than or equal to 30 mg/kg/day (approximately 0.4-fold the AUC at the MRHD of 800 mg/day). Total litter resorption was seen at 300 mg/kg/day (approximately 0.8-fold the AUC at the MRHD of 800 mg/day). Postimplantation loss, embryolethality, and decreased fetal body weights were noted in females administered doses greater than or equal to 10 mg/kg/day (approximately 0.3-fold the AUC at the MRHD of 800 mg/day).

In embryo-fetal developmental toxicity studies in rats and rabbits, oral pazopanib was administered to pregnant animals during organogenesis. In rats, dose levels of greater than or equal to 3 mg/kg/day (approximately 0.1-fold the AUC at the MRHD of 800 mg/day) resulted in teratogenic effects, including cardiovascular malformations (retroesophageal subclavian artery, missing innominate artery, changes in the aortic arch), incomplete or absent ossification, increases in postimplantation loss, embryolethality and reduced fetal body weight. In rabbits, maternal toxicity, increased postimplantation loss and abortion were observed at doses greater than or equal to 30 mg/kg/day (approximately 0.007-fold the AUC at the MRHD of 800 mg/day). In addition, severe maternal body weight loss and 100% litter loss were observed at doses greater than or equal to 100 mg/kg/day (0.02-fold the AUC at the MRHD of 800 mg/day), while fetal weight was reduced at doses greater than or equal to 3 mg/kg/day (AUC not calculated).

8.2 Lactation

Risk Summary

There is no data on the presence of pazopanib or its metabolites in human milk or their effects on the breastfed infant or milk production. Because of the potential for serious adverse reactions in breastfed infants, advise women not to breastfeed during treatment with VOTRIENT and for 2 weeks after the final dose.

8.3 Females and Males of Reproductive Potential

VOTRIENT can cause fetal harm when administered to a pregnant woman [see Use in Specific Populations (8.1)].

Pregnancy Testing

Verify pregnancy status of females of reproductive potential prior to starting treatment with VOTRIENT.

Contraception

Females

Advise females of reproductive potential to use effective contraception during treatment with VOTRIENT and for at least 2 weeks after the last dose.

Males

Advise males (including those who have had vasectomies) with female partners of reproductive potential to use condoms during treatment with VOTRIENT and for at least 2 weeks after the last dose.

Infertility

Based on findings from animal studies, VOTRIENT may impair fertility in females and males of reproductive potential while receiving treatment [see Nonclinical Toxicology (13.1)].

8.4 Pediatric Use

The safety and effectiveness of VOTRIENT in pediatric patients have not been established.

VOTRIENT is not indicated for use in pediatric patients [see Warnings and Precautions (5.18)]. Based on its mechanism of action, pazopanib may have severe effects on organ growth and maturation during early postnatal development. Administration of pazopanib to juvenile rats < 21 days old resulted in toxicity to the lungs, liver, heart, and kidney and in death at doses significantly lower than the clinically recommended dose or doses tolerated in older animals (see Juvenile Animal Toxicity Data).

The safety and efficacy of VOTRIENT or an unapproved pazopanib formulation were investigated but not established in two open-label studies: a study in 37 pediatric patients 2 to < 17 years with recurrent or refractory solid tumors [NCT00929903] and a study in 46 pediatric patients 1 year to < 17 years with refractory solid tumors, including sarcoma [NCT01956669]. Meaningful anti-tumor activity was not observed in these studies.

Juvenile Animal Toxicity Data

In rats, weaning occurs at Day 21 postpartum which approximately equates to a human pediatric age of 2 years. In a juvenile animal toxicology study performed in rats, when animals were dosed from Day 9 through Day 14 postpartum (pre-weaning), pazopanib caused abnormal organ growth/maturation in the kidney, lung, liver, and heart at approximately 0.1-fold the AUC in adults at the MRHD of 800 mg/day of VOTRIENT. At approximately 0.4-fold the AUC in adults at the MRHD of 800 mg/day, pazopanib administration resulted in mortality.

In repeat-dose toxicology studies in rats, including 4-week, 13-week, and 26-week administration, toxicities in bone, teeth, and nail beds were observed at doses greater than or equal to 3 mg/kg/day (approximately 0.07-fold the AUC at the MRHD of 800 mg/day). Doses of 300 mg/kg/day (approximately 0.8-fold the AUC at the MRHD of 800 mg/day) were not tolerated in 13- and 26-week studies and animals required dose reductions due to body weight loss and morbidity. Hypertrophy of epiphyseal growth plates, nail abnormalities (including broken, overgrown, or absent nails) and tooth abnormalities in growing incisor teeth (including excessively long, brittle, broken, and missing teeth, and dentine and enamel degeneration and thinning) were observed in rats at doses greater than or equal to 30 mg/kg/day (approximately 0.35-fold the AUC at the MRHD of 800 mg/day) at 26 weeks, with the onset of tooth and nail bed alterations noted clinically after 4 to 6 weeks. Similar findings were noted in repeat-dose studies in juvenile rats dosed with pazopanib beginning Day 21 postpartum (post-weaning). In the post-weaning animals, the occurrence of changes in teeth and bones occurred earlier and with greater severity than in older animals. There was evidence of tooth degeneration and decreased bone growth at doses greater than or equal to 30 mg/kg (approximately 0.1- to 0.2-fold the AUC at the MRHD of 800 mg/day). Pazopanib exposure in juvenile rats was lower than that seen at the same dose levels in adult animals, based on comparative AUC values. At pazopanib doses approximately 0.5- to 0.7-fold the AUC at the MRHD of 800 mg/day, decreased bone growth in juvenile rats persisted even after the end of the dosing period. Finally, despite lower pazopanib exposures than those reported in adult animals or adult humans, juvenile animals administered 300 mg/kg/dose pazopanib required dose reduction within 4 weeks of dosing initiation due to significant toxicity, although adult animals could tolerate this same dose for at least 3 times as long [see Warnings and Precautions (5.18)].

8.5 Geriatric Use

In pooled clinical trials with VOTRIENT, 30% of 2080 patients were aged ≥ 65 years. More patients ≥ 65 years had ALT elevations > 3 × ULN compared to patients < 65 years (23% versus 18%) [see Warnings and Precautions (5.1)].

In the RCC trials, 33% of 586 patients were aged ≥ 65 years. No overall differences in safety or effectiveness of VOTRIENT were observed between these patients and younger patients.

In the STS trials, 24% of 382 patients were aged ≥ 65 years. Patients aged ≥ 65 years had a higher incidence of Grade 3 or 4 fatigue (19% versus 12% for patients aged < 65 years), hypertension (10% versus 6%), decreased appetite (11% versus 2%), ALT elevations (3% versus 2%) and AST elevations (4% versus 1%). In the randomized STS trial (VEG110727), no overall differences in effectiveness of VOTRIENT were observed between patients aged ≥ 65 years and younger patients.

8.6 Renal Impairment

No dose adjustment is recommended for patients with renal impairment. VOTRIENT has not been studied in patients with severe renal impairment or in patients undergoing peritoneal dialysis or hemodialysis.

8.7 Hepatic Impairment

No dose adjustment is required in patients with mild hepatic impairment (either total bilirubin ≤ ULN and ALT > ULN or bilirubin > 1 to 1.5 × ULN and any ALT value). VOTRIENT is not recommended in patients with moderate (total bilirubin > 1.5 to 3 × ULN and any ALT value) and severe (total bilirubin > 3 × ULN and any ALT value) hepatic impairment [see Dosage and Administration (2.3), Clinical Pharmacology (12.3)].

10 OVERDOSAGE

Dose-limiting toxicity (Grade 3 fatigue) and Grade 3 hypertension were each observed in 1 of 3 patients dosed at 2,000 mg daily (2.5 times the recommended dose) and 1,000 mg daily (1.25 times the recommended dose), respectively.

Provide general supportive measures to manage an overdose. Hemodialysis is not expected to enhance the elimination of VOTRIENT because pazopanib is not significantly renally excreted and is highly bound to plasma proteins.

11 DESCRIPTION

Pazopanib is a kinase inhibitor. Pazopanib is presented as the hydrochloride salt, with the chemical name 5-[[4-[(2,3-dimethyl-2H-indazol-6-yl)methylamino]-2-pyrimidinyl]amino]-2-methylbenzenesulfonamide monohydrochloride. It has the molecular formula C21H23N7O2S•HCl and a molecular weight of 473.99 g/mol. Pazopanib hydrochloride has the following chemical structure:

Pazopanib hydrochloride is a white to slightly yellow solid. It is very slightly soluble at pH 1 and practically insoluble above pH 4 in aqueous media.

VOTRIENT tablets are for oral use. Each 200-mg tablet of VOTRIENT contains 200 mg of pazopanib equivalent to 216.7 mg of pazopanib hydrochloride. The inactive ingredients of VOTRIENT are: Tablet Core: magnesium stearate, microcrystalline cellulose, povidone, and sodium starch glycolate. Coating: Gray or pink film-coat: hypromellose, iron oxide black, macrogol/polyethylene glycol 400 (PEG 400), polysorbate 80, and titanium dioxide.

12 CLINICAL PHARMACOLOGY

12.1 Mechanism of Action

Pazopanib is a multi-tyrosine kinase inhibitor of vascular endothelial growth factor receptor (VEGFR)-1, VEGFR-2, VEGFR-3, platelet-derived growth factor receptor (PDGFR)-α and -β, fibroblast growth factor receptor (FGFR)-1 and -3, cytokine receptor (Kit), interleukin-2 receptor-inducible T-cell kinase (Itk), lymphocyte-specific protein tyrosine kinase (Lck), and transmembrane glycoprotein receptor tyrosine kinase (c-Fms). In vitro, pazopanib inhibited ligand-induced autophosphorylation of VEGFR-2, Kit, and PDGFR-β receptors. In vivo, pazopanib inhibited VEGF-induced VEGFR-2 phosphorylation in mouse lungs, angiogenesis in a mouse model, and the growth of some human tumor xenografts in mice.

12.2 Pharmacodynamics

Increases in blood pressure have been observed and are related to steady-state trough plasma pazopanib concentrations.

Cardiac Electrophysiology

The QT prolongation potential of pazopanib was assessed in a randomized, blinded, parallel trial (N = 96) using moxifloxacin as a positive control. VOTRIENT 800 mg orally under fasting conditions was administered on Days 2 to 8 and 1,600 mg was administered on Day 9 after a meal in order to increase exposure to pazopanib and its metabolites. No large changes (i.e., > 20 msec) in QTc interval following exposure to pazopanib were detected in this QT trial. The trial was not able to exclude small changes (< 10 msec) in QTc interval, because assay sensitivity below this threshold (< 10 msec) was not established in this trial [see Warnings and Precautions (5.2)].

12.3 Pharmacokinetics

The recommended dosage of 800 mg once daily results in mean AUC of 1,037 mcg•h/mL and Cmax of 58.1 mcg/mL. There was no consistent increase in AUC or Cmax at pazopanib doses above 800 mg.

Administration of a single 400-mg crushed tablet increased AUC0-72h by 46% and Cmax by approximately 2-fold and decreased Tmax by approximately 2 hours compared with administration of the whole tablet [see Dosage and Administration (2.1)].

Absorption

The median time to achieve peak concentrations was 2 to 4 hours after a dose.

Effect of Food

Systemic exposure to pazopanib is increased when administered with food. Administration of pazopanib with a high-fat (approximately 50% fat) or low-fat (approximately 5% fat) meal results in an approximately 2-fold increase in AUC and Cmax.

Distribution

Binding of pazopanib to human plasma protein in vivo was > 99% with no concentration dependence over the range of 10 to 100 mcg/mL. In vitro studies suggest that pazopanib is a substrate for P-gp and BCRP.

Elimination

Pazopanib has a mean half-life of 31 hours after administration of the recommended dose of 800 mg.

Metabolism

In vitro studies demonstrated that pazopanib is metabolized by CYP3A4 with a minor contribution from CYP1A2 and CYP2C8.

Excretion

Elimination is primarily via feces with renal elimination accounting for < 4% of the administered dose.

Specific Populations

Patients with Hepatic Impairment

Table 7 presents a comparison of the median steady-state Cmax and the median AUC0-24h values for patients with normal, mild, moderate and severe hepatic impairment.

The median steady-state of pazopanib Cmax and AUC0-24h after a once-daily dose of 800 mg in patients with mild impairment were in a similar range as the median steady-state Cmax and median AUC0-24h in patients with no hepatic impairment.

The maximum tolerated pazopanib dose in patients with moderate hepatic impairment was 200 mg once daily. The median steady-state Cmax and the median AUC0-24h were approximately 43% and 29%, respectively, of the corresponding median values after administration of 800 mg once daily in patients with no hepatic impairment.

The median steady-state Cmax and the median AUC0-24h were approximately 18% and 15%, respectively, of the corresponding median values after administration of 800 mg once daily in patients with no hepatic impairment.

Table 7. Pharmacokinetic Parameters of Pazopanib in Patients with Hepatic Impairment
 | No hepatic impairment | Mild hepatic impairment (total bilirubin ≤ ULN and ALT > ULN or total bilirubin > 1 to 1.5 × ULN and any ALT value) | Moderate hepatic impairment (total bilirubin > 1.5 to 3 × ULN and any ALT value) | Severe hepatic impairment (total bilirubin > 3 × ULN and any ALT value)
Dose | 800 mg once daily | 800 mg once daily | 200 mg once daily | 200 mg once daily
Median steady-state Cmax (range) mcg/mL | 52 (17 to 86) | 34 (11 to 104) | 22 (4.2 to 33) | 9.4 (2.4 to 24)
Median AUC0-24h (range) mcg•h/mL | 888 (346 to 1482) | 774 (215 to 2034) | 257 (66 to 488) | 131 (47 to 473)
Abbreviations: ALT, alanine aminotransferase; AUC, area under the curve; Cmax, maximum concentration; ULN, upper limit of normal.

Drug Interactions Studies

Clinical Studies

Strong CYP3A4 Inhibitor: Coadministration of multiple doses of oral VOTRIENT 400 mg with multiple doses of oral ketoconazole 400 mg (strong CYP3A4/P-gp inhibitor) resulted in a 1.7-fold increase in the AUC0-24h and a 1.5-fold increase in the Cmax of pazopanib [see Dosage and Administration (2.4), Drug Interactions (7.1)].

Weak CYP3A4 Inhibitor: Coadministration of 1,500 mg lapatinib, a substrate and weak inhibitor of CYP3A4, P-gp, and BCRP, with VOTRIENT 800 mg resulted in an approximately 50% to 60% increase in mean pazopanib AUC0-24h and Cmax.

CYP1A2, CYP2C9 and CYP2C19 Substrates: Clinical studies, using VOTRIENT 800 mg once daily, have demonstrated that pazopanib does not have a clinically relevant effect on the pharmacokinetics of caffeine (CYP1A2 probe substrate), warfarin (CYP2C9 probe substrate), or omeprazole (CYP2C19 probe substrate) in patients with cancer.

CYP3A4, CYP2D6, and CYP2C8 Substrates: Coadministration of VOTRIENT resulted in an increase of approximately 30% in the mean AUC and Cmax of midazolam (CYP3A4 probe substrate) and increases of 33% to 64% in the ratio of dextromethorphan to dextrorphan concentrations in the urine after oral administration of dextromethorphan (CYP2D6 probe substrate). Coadministration of VOTRIENT 800 mg once daily and paclitaxel 80 mg/m^2 (CYP3A4 and CYP2C8 substrate) once weekly resulted in a mean increase of 26% and 31% in paclitaxel AUC and Cmax, respectively [see Drug Interactions (7.2)].

Gastric Acid-Reducing Agents: Coadministration of VOTRIENT with esomeprazole, a PPI, decreased the exposure of pazopanib by approximately 40% (AUC and Cmax) [see Dosage and Administration (2.4), Drug Interactions (7.4)].

In Vitro Studies

In vitro studies with human liver microsomes showed that pazopanib inhibited the activities of CYP enzymes 1A2, 3A4, 2B6, 2C8, 2C9, 2C19, 2D6, and 2E1. Potential induction of human CYP3A4 was demonstrated in an in vitro human pregnane X receptor (PXR) assay.

In vitro studies also showed that pazopanib inhibits UGT1A1 and organic anion-transporting polypeptide (OATP1B1) with IC50s of 1.2 and 0.79 μM, respectively.

12.5 Pharmacogenomics

Pazopanib can increase serum total bilirubin levels [see Warnings and Precautions (5.1)]. In vitro studies showed that pazopanib inhibits UGT1A1, which glucuronidates bilirubin for elimination. A pooled pharmacogenetic analysis of 236 white patients who received VOTRIENT showed that the (TA)7/(TA)7 genotype (UGT1A1*28/*28) (underlying genetic susceptibility to Gilbert’s syndrome) was associated with a statistically significant increase in the incidence of hyperbilirubinemia relative to the (TA)6/(TA)6 and (TA)6/(TA)7 genotypes.

In a pooled pharmacogenetic analysis of data from 31 clinical studies of pazopanib administered as either monotherapy or in combination with other agents, ALT > 3 × ULN (Grade 2) occurred in 32% (42/133) of HLA-B*57:01 allele carriers and in 19% (397/2101) of non-carriers and ALT > 5 × ULN (Grade 3) occurred in 19% (25/133) of HLA-B*57:01 allele carriers and in 10% (213/2101) of non-carriers. In this dataset, 6% (133/2234) of the patients carried the HLA-B*57:01 allele [see Warnings and Precautions (5.1)].

13 NONCLINICAL TOXICOLOGY

13.1 Carcinogenesis, Mutagenesis, Impairment of Fertility

The carcinogenic potential of pazopanib was evaluated in CD-1 mice, and Sprague-Dawley rats. Administration of pazopanib to mice for 2 years did not result in increased incidence of neoplasms at doses up to 100 mg/kg/day (approximately 1.4-fold the AUC at the MRHD of 800 mg/day). Administration of pazopanib to rats for 2 years resulted in findings of duodenal adenocarcinoma in males at 30 mg/kg/day (approximately 0.3-fold the AUC at the MRHD of 800 mg/day) and in females at greater than or equal to 10 mg/kg/day (approximately 0.3-fold the AUC at the MRHD of 800 mg/day). The human relevance of these neoplastic findings is unclear.

Pazopanib did not induce mutations in the microbial mutagenesis (Ames) assay and was not clastogenic in both the in vitro cytogenetic assay using primary human lymphocytes and in the in vivo rat micronucleus assay.

In an oral female fertility and early embryonic development study, female rats were administered pazopanib at least 15 days prior to mating, and for 6 days after mating. Pazopanib did affect fertility in female rats. Reduced fertility, including increased pre-implantation loss and early resorptions, were noted at dosages greater than or equal to 30 mg/kg/day (approximately 0.4-fold the AUC at the MRHD of 800 mg/day). Decreased corpora lutea and increased cysts were noted in mice given greater than or equal to 100 mg/kg/day for 13 weeks and ovarian atrophy was noted in rats given greater than or equal to 300 mg/kg/day for 26 weeks (approximately 1.3 and 0.85-fold the AUC at the MRHD of 800 mg/day). Decreased corpora lutea was also noted in monkeys given 500 mg/kg/day for up to 34 weeks (approximately 0.4-fold the AUC at the MRHD of 800 mg/day).

Pazopanib did not affect mating or fertility in male rats. However, there were reductions in sperm production rates and testicular sperm concentrations at doses greater than or equal to 3 mg/kg/day, epididymal sperm concentrations at doses greater than or equal to 30 mg/kg/day, and sperm motility at greater than or equal to 100 mg/kg/day following 15 weeks of dosing. Following 15 and 26 weeks of dosing, there were decreased testicular and epididymal weights at doses of greater than or equal to 30 mg/kg/day (approximately 0.35-fold the AUC at the MRHD of 800 mg/day); atrophy and degeneration of the testes with aspermia, hypospermia, and cribiform change in the epididymis was also observed at this dose in the 6-month toxicity studies in male rats.

14 CLINICAL STUDIES

14.1 Renal Cell Carcinoma

The efficacy of VOTRIENT was evaluated in VEG105192, a randomized, double-blind, placebo-controlled, multicenter trial (NCT00387764). Patients with locally advanced and/or metastatic RCC who had received either no prior therapy or one prior cytokine-based systemic therapy were randomized (2:1) to receive VOTRIENT 800 mg once daily or placebo once daily. Eligible subjects were stratified according to the following 3 stratification factors: baseline ECOG performance status 0 versus 1; prior nephrectomy yes versus no; and prior systemic therapy for advanced RCC: treatment-naïve versus one prior cytokine-based therapy. The major efficacy outcome measure was progression-free survival (PFS). Additional outcome measures were overall survival (OS), overall response rate (ORR), and duration of response.

Of the total of 435 patients enrolled in this trial, 233 patients had no prior systemic therapy (treatment-naïve subgroup) and 202 patients received one prior IL-2 or INFα-based therapy (cytokine-pretreated subgroup). The baseline demographic and disease characteristics were balanced between the arms receiving VOTRIENT and placebo. The majority of patients were male (71%) with a median age of 59 years. Eighty-six percent of patients were white, 14% were Asian, and < 1% were other. Forty-two percent were ECOG performance status 0 and 58% were ECOG performance status 1. All patients had clear cell histology (90%) or predominantly clear cell histology (10%). Approximately 50% of all patients had 3 or more organs involved with metastatic disease. The most common metastatic sites at baseline were lung (74%), lymph nodes (56%), bone (27%), and liver (25%).

A similar proportion of patients in each arm were treatment-naïve and cytokine-pretreated (see Table 8). In the cytokine-pretreated subgroup, the majority (75%) had received interferon-based treatment. Similar proportions of patients in each arm had prior nephrectomy (89% and 88% for VOTRIENT and placebo, respectively).

The analysis of the primary endpoint PFS was based on disease assessment by independent radiological review in the entire trial population. Efficacy results are presented in Table 8 and Figure 1.

Table 8. Efficacy Results in RCC Patients by Independent Assessment in VEG105192
 |  |  | HR
Endpoint/Trial population | VOTRIENT | Placebo | (95% CI)
PFS
Overall ITT | N = 290 | N = 145
Median (months) | 9.2 | 4.2 | 0.46a (0.34, 0.62)
Treatment-naïve subgroup | N = 155 (53%) | N = 78 (54%)
Median (months) | 11.1 | 2.8 | 0.40 (0.27, 0.60)
Cytokine pre-treated subgroup | N = 135 (47%) | N = 67 (46%)
Median (months) | 7.4 | 4.2 | 0.54 (0.35, 0.84)
Response rate (CR + PR) | N = 290 | N = 145
% (95% CI) | 30 (25.1, 35.6) | 3 (0.5, 6.4) | –
Duration of response
Median (weeks) (95% CI) | 58.7 (52.1, 68.1) | –b
Abbreviations: CI, confidence interval; CR, complete response; HR, hazard ratio; ITT, intent-to-treat; PFS, progression-free survival; PR, partial response; RCC, renal cell carcinoma.
a P value < 0.001.
bThere were only 5 objective responses.

Figure 1. Kaplan-Meier Curve for Progression-free Survival in RCC by Independent Assessment for the Overall Population (Treatment-naïve and Cytokine Pre-treated Populations) in VEG105192

At the protocol-specified final analysis of OS, the median OS was 22.9 months for patients randomized to VOTRIENT and 20.5 months for the placebo arm [HR = 0.91 (95% CI: 0.71, 1.16)]. The median OS for the placebo arm includes 79 patients (54%) who discontinued placebo treatment because of disease progression and crossed over to treatment with VOTRIENT. In the placebo arm, 95 (66%) patients received at least one systemic anticancer treatment after progression compared with 88 (30%) patients randomized to VOTRIENT.

14.2 Soft Tissue Sarcoma

The efficacy of VOTRIENT was evaluated in VEG110727, a randomized, double-blind, placebo-controlled, multicenter trial (NCT00753688). Patients with metastatic STS who had received prior chemotherapy, including anthracycline treatment, or were unsuited for such therapy, were randomized (2:1) to receive VOTRIENT 800 mg once daily or placebo. Patients with gastrointestinal stromal tumors (GIST) or adipocytic sarcoma were excluded from the trial. Randomization was stratified by the factors of WHO performance status (WHO PS) 0 or 1 at baseline and the number of lines of prior systemic therapy for advanced disease (0 or 1 versus 2+). The major efficacy outcome measure was PFS assessed by independent radiological review. Additional outcome measures were OS, ORR, and duration of response.

The majority of patients were female (59%) with a median age of 55 years. Seventy-two percent of patients were white, 22% were Asian, and 6% were other. Forty-three percent of patients had leiomyosarcoma, 10% had synovial sarcoma, and 47% had other soft tissue sarcomas. Fifty-six percent of patients had received 2 or more lines of prior systemic therapy and 44% had received 0 or 1 lines of prior systemic therapy.

Efficacy results are presented in Table 9 and Figure 2.

Table 9. Efficacy Results in STS Patients by Independent Assessment in VEG110727
 |  |  | HR
Endpoint/Trial population | VOTRIENT | Placebo | (95% CI)
PFS
Overall ITT | N = 246 | N = 123 | 0.35a
Median (months) | 4.6 | 1.6 | (0.26, 0.48)
Leiomyosarcoma subgroup | N = 109 | N = 49 | 0.37
Median (months) | 4.6 | 1.9 | (0.23, 0.60)
Synovial sarcoma subgroup | N = 25 | N = 13 | 0.43
Median (months) | 4.1 | 0.9 | (0.19, 0.98)
‘Other soft tissue sarcoma’ subgroup | N = 112 | N = 61 | 0.39
Median (months) | 4.6 | 1.0 | (0.25, 0.60)
Response rate (CR + PR)
% (95% CI) | 4 (2.3, 7.9)b | 0 (0.0, 3.0) | –
Duration of response
Median (months) (95% CI) | 9.0 (3.9, 9.2)
Abbreviations: CI, confidence interval; CR, complete response; HR, hazard ratio; ITT, intent-to-treat; PFS, progression-free survival; PR, partial response; STS, soft tissue sarcoma.
a P value < 0.001.
bThere were 11 partial responses and 0 complete responses.

Figure 2. Kaplan-Meier Curve for Progression-free Survival in STS by Independent Assessment for the Overall Population in VEG110727

At the protocol-specified final analysis of OS, the median OS was 12.6 months for patients randomized to VOTRIENT and 10.7 months for the placebo arm [HR = 0.87 (95% CI: 0.67, 1.12)].

16 HOW SUPPLIED/STORAGE AND HANDLING

VOTRIENT 200 mg tablets are supplied as modified capsule-shaped, gray or pink, film-coated with ‘GS JT’ debossed on one side and are available in:

- Bottles of 120 tablets: NDC 0078-0670-66 (gray tablets), NDC 0078-1077-66 (pink tablets)

Store at 20°C to 25°C (68°F to 77°F), excursions permitted between 15°C and 30°C (59°F and 86°F) [see USP Controlled Room Temperature].

17 PATIENT COUNSELING INFORMATION

Advise the patient to read the FDA-approved patient labeling (Medication Guide).

- Hepatic Toxicity: Inform patients that periodic laboratory testing will be performed. Advise patients to report signs and symptoms of liver dysfunction to their healthcare provider right away [see Warnings and Precautions (5.1)].
- QT Prolongation and Torsades de Pointes: Inform patients that ECG monitoring may be performed. Advise patients to inform their physicians of concomitant medications [see Warnings and Precautions (5.2)].
- Interstitial Lung Disease/Pneumonitis: Advise patients to report pulmonary signs or symptoms indicative of interstitial lung disease (ILD) or pneumonitis [see Warnings and Precautions (5.9)].
- Cardiac Dysfunction: Advise patients to report hypertension or signs and symptoms of congestive heart failure [see Warnings and Precautions (5.3)].
- Hemorrhagic Events: Advise patients to report unusual bleeding [see Warnings and Precautions (5.4)].
- Arterial Thromboembolic Events: Advise patients to report signs or symptoms of an arterial thrombosis [see Warnings and Precautions (5.5)].
- Pneumothorax and Venous Thromboembolic Events: Advise patients to report new onset of dyspnea, chest pain, or localized limb edema [see Warnings and Precautions (5.6), Adverse Reactions (6.1)].
- Posterior Reversible Encephalopathy Syndrome: Advise patients to inform their doctor if they have worsening of neurological function consistent with PRES (headache, seizure, lethargy, confusion, blindness, and other visual and neurologic disturbances) [see Warnings and Precautions (5.10)].
- Hypertension: Advise patients to monitor blood pressure early in the course of therapy and frequently thereafter and report increases of blood pressure or symptoms, such as blurred vision, confusion, severe headache, or nausea and vomiting [see Warnings and Precautions (5.11)].
- Gastrointestinal Perforation and Fistula: Advise patients to report signs and symptoms of a GI perforation or fistula [see Warnings and Precautions (5.8)].
- Risk of Impaired Wound Healing: Advise patients that VOTRIENT may impair wound healing. Advise patients to inform their healthcare provider of any scheduled surgical procedure [see Warnings and Precautions (5.12)].
- Hypothyroidism and Proteinuria: Inform patients that thyroid function testing and urinalysis will be performed during treatment [see Warnings and Precautions (5.13, 5.14)].
- Tumor Lysis Syndrome: Advise patients to contact their healthcare provider promptly to report any signs and symptoms of TLS, such as abnormal heart rhythm, seizure, confusion, muscle cramps or spasms, or a decrease in urine output [see Warnings and Precautions (5.15)].
- Infection: Advise patients to promptly report any signs or symptoms of infection [see Warnings and Precautions (5.16)].
- Embryo-Fetal Toxicity: Advise female patients to inform their healthcare provider of a known or suspected pregnancy during treatment with VOTRIENT. Inform female patients of the risk to a fetus and the potential loss of the pregnancy [see Warnings and Precautions (5.19), Use in Specific Populations (8.1)].
  Advise females of reproductive potential to use effective contraception during treatment and for at least 2 weeks after the last dose of VOTRIENT. Advise male patients with female partners of reproductive potential to use condoms during treatment with VOTRIENT and for at least 2 weeks after the last dose [see Warnings and Precautions (5.19), Use in Specific Populations (8.3)].
- Lactation: Advise women not to breastfeed during treatment with VOTRIENT and for 2 weeks after the last dose [see Use in Specific Populations (8.2)].
- Infertility: Advise males and females of reproductive potential that VOTRIENT may impair fertility [see Use in Specific Populations (8.3)].
- Gastrointestinal Adverse Reactions: Advise patients on how to manage nausea, vomiting, and diarrhea and to notify their healthcare provider if moderate-to-severe vomiting or diarrhea occurs or if there is a decrease in oral intake [see Adverse Reactions (6.1)].
- Depigmentation: Advise patients that depigmentation of the hair or skin may occur during treatment with VOTRIENT [see Adverse Reactions (6.1)].
- Drug Interactions: Advise patients to inform their healthcare providers of all concomitant medications, vitamins, or dietary and herbal supplements [see Drug Interactions (7)].
- Dosage and Administration: Advise patients to take VOTRIENT without food (at least 1 hour before or 2 hours after a meal) [see Dosage and Administration (2.1)].

Distributed by:
Novartis Pharmaceuticals Corporation
East Hanover, New Jersey 07936

© Novartis

T2024-07

MEDICATION GUIDE
VOTRIENT® (VO-tree-ent)
(pazopanib)
tablets

What is the most important information I should know about VOTRIENT?
VOTRIENT can cause severe liver problems, including death. Your healthcare provider will do blood tests to check
your liver before you start and while you take VOTRIENT.
Tell your healthcare provider right away if you get any of these signs of liver problems during treatment with VOTRIENT:

○ yellowing of your skin or the whites of your eyes (jaundice)

○ loss of appetite

○ dark urine

○ pain on the right side of your stomach area (abdomen)

○ tiredness

○ bruise easily

○ nausea or vomiting

Your healthcare provider may need to prescribe a lower dose of VOTRIENT for you or tell you to stop taking VOTRIENT if you develop liver problems during treatment.

What is VOTRIENT?
VOTRIENT is a prescription medicine used to treat adults with:

- advanced renal cell cancer (RCC)
- advanced soft tissue sarcoma (STS) who have received chemotherapy in the past

It is not known if VOTRIENT is effective in treating certain soft tissue sarcomas or certain gastrointestinal tumors.
It is not known if VOTRIENT is safe and effective in children under 18 years of age.

What should I tell my healthcare provider before taking VOTRIENT?
Before taking VOTRIENT, tell your healthcare provider about all of your medical conditions, including if you:

- have or had liver problems. You may need a lower dose of VOTRIENT, or your healthcare provider may prescribe a different medicine to treat your advanced renal cell cancer or advanced soft tissue sarcoma.
- have high blood pressure
- have heart problems or an irregular heartbeat, including QT prolongation
- have a history of a stroke
- have headaches, seizures, or vision problems
- have coughed up blood in the last 6 months
- had bleeding of your stomach or intestines in the last 6 months
- have a history of a tear (perforation) in your stomach or intestine, or an abnormal connection between two parts of your gastrointestinal tract (fistula)
- have had blood clots in a vein or in the lung
- have thyroid problems
- had recent surgery or are going to have surgery. You should stop taking VOTRIENT at least 1 week before scheduled surgery because VOTRIENT may affect healing after surgery. Do not take VOTRIENT for at least 2 weeks following major surgery and until your wound heals adequately. Your healthcare provider should tell you when you may start taking VOTRIENT again after surgery.
- have problems with your kidney function
- are pregnant or plan to become pregnant. VOTRIENT can harm your unborn baby. Your healthcare provider should check to see if you are pregnant before you start taking VOTRIENT. You should not become pregnant while you are taking VOTRIENT. You should use effective birth control during treatment with VOTRIENT and for at least 2 weeks after your final dose of VOTRIENT. Talk to your healthcare provider about types of birth control that may be right for you during this time.
- are a male (including one who has had a vasectomy) with a sexual partner who is pregnant, think that they may be pregnant, or who could become pregnant (including those who use other forms of birth control). You should use condoms during sexual intercourse during treatment with VOTRIENT and for at least 2 weeks after the last dose of VOTRIENT.
- are breastfeeding or plan to breastfeed. It is not known if VOTRIENT passes into your breast milk. Do not breastfeed during treatment with VOTRIENT and for 2 weeks after the final dose.

Tell your healthcare provider about all the medicines you take, including prescription and over-the-counter medicines, vitamins, and herbal supplements. VOTRIENT may affect the way other medicines work and other medicines may affect how VOTRIENT works.

Especially, tell your healthcare provider if you:

- take medicines that can affect how your liver enzymes work, such as:

○ certain antibiotics (used to treat infections)

○ certain medicines used to treat depression

○ certain medicines used to treat HIV-1

○ medicines used to treat irregular heartbeats

- take a medicine that contains simvastatin to treat high cholesterol levels
- take medicines that reduce stomach acid (e.g., esomeprazole)
- drink grapefruit juice

Ask your healthcare provider if you are not sure if your medicine is one that is listed above.
Know the medicines you take. Keep a list of them and show it to your healthcare provider and pharmacist when you get a new medicine.

How should I take VOTRIENT?

- Take VOTRIENT exactly as your healthcare provider tells you. Your healthcare provider will tell you how much VOTRIENT to take.
- Your healthcare provider may change your dose.
- Take VOTRIENT on an empty stomach, at least 1 hour before or 2 hours after food.
- Swallow VOTRIENT tablets whole. Do not crush VOTRIENT tablets. It may increase the amount of VOTRIENT in your body.
- Do not eat grapefruit or drink grapefruit juice during treatment with VOTRIENT. Grapefruit products may increase the amount of VOTRIENT in your body.
- If you miss a dose, take it as soon as you remember. Do not take it if it is close (within 12 hours) to your next dose. Just take the next dose at your regular time. Do not take more than 1 dose of VOTRIENT at a time.
- Your healthcare provider will test your urine, blood, and heart before you start and while you take VOTRIENT.

What are the possible side effects of VOTRIENT?
VOTRIENT may cause serious side effects, including:

- See “What is the most important information I should know about VOTRIENT?”
- irregular or fast heartbeat or fainting
- heart failure. This is a condition where your heart does not pump as well as it should and may cause you to have shortness of breath.
- bleeding problems. These bleeding problems may be severe and cause death.
  Symptoms may include: unusual bleeding, bruising, or wounds that do not heal.
- heart attack or stroke. Heart attack and stroke can happen with VOTRIENT and may cause death.
  Symptoms may include: chest pain or pressure, pain in your arms, back, neck or jaw, shortness of breath, numbness or weakness on one side of your body, trouble talking, headache, or dizziness.
- blood clots. Blood clots may form in a vein, especially in your legs (deep vein thrombosis or DVT). Pieces of a blood clot may travel to your lungs (pulmonary embolism). This may be life-threatening and cause death.
  Symptoms may include: new chest pain, trouble breathing or shortness of breath that starts suddenly, leg pain, and swelling of the arms and hands, or legs and feet, a cool or pale arm or leg.
- Thrombotic microangiopathy (TMA), including thrombotic thrombocytopenia purpura (TTP) and hemolytic uremic syndrome (HUS). TMA is a condition involving blood clots that can happen while taking VOTRIENT. TMA is accompanied by a decrease in red blood cells and cells that are involved in clotting. TMA may harm organs, such as the brain and kidneys.
- tear in your stomach or intestinal wall (perforation) or an abnormal connection between two parts of your gastrointestinal tract (fistula).
  Symptoms may include: pain, swelling in your stomach area, vomiting blood, and black sticky stools.
- lung problems. VOTRIENT may cause lung problems that may lead to death. Tell your healthcare provider right away if you get a cough that will not go away or shortness of breath.
- Posterior Reversible Encephalopathy Syndrome (PRES). PRES is a condition that can happen while taking VOTRIENT that may cause death.
  Symptoms may include: headaches, seizures, lack of energy, confusion, high blood pressure, loss of speech, blindness or changes in vision, and problems thinking.
- high blood pressure. High blood pressure can happen with VOTRIENT, including a sudden and severe rise in blood pressure which may be life-threatening. These blood pressure increases usually happen in the first several months of treatment. Your blood pressure should be well controlled before you start taking VOTRIENT. Your healthcare provider should begin checking your blood pressure within 1 week of you starting VOTRIENT and often during treatment to make sure that your blood pressure is well controlled.
  Have someone call your healthcare provider or get medical help right away for you, if you get symptoms of a severe increase in blood pressure, including: severe chest pain, severe headache, blurred vision, confusion, nausea and vomiting, severe anxiety, shortness of breath, seizures, or you pass out (become unconscious).
- thyroid problems. Your healthcare provider should check you for this during treatment with VOTRIENT.
- Tumor lysis syndrome (TLS). TLS is a condition that can happen during treatment with VOTRIENT that may cause death. TLS is caused by a fast breakdown of cancer cells. Your healthcare provider may do a blood test to check you for TLS. Call your healthcare provider or get emergency medical help right away if you develop any of these symptoms during treatment with VOTRIENT: irregular heartbeat, seizures, confusion, muscle cramps or spasms, or a decrease in urine output.
- protein in your urine. Your healthcare provider will check you for this problem. If there is too much protein in your urine, your healthcare provider may tell you to stop taking VOTRIENT.
- serious infections. Serious infections can happen with VOTRIENT and can cause death.
  Symptoms of an infection may include: fever, cold symptoms, such as runny nose or sore throat that do not go away, flu symptoms, such as cough, tiredness, and body aches, pain when urinating, cuts, scrapes or wounds that are red, warm, swollen or painful.
- collapsed lung (pneumothorax). A collapsed lung can happen with VOTRIENT. Air may get trapped in the space between your lung and chest wall. This may cause you to have shortness of breath.

Call your healthcare provider right away if you have any of the symptoms listed above.
The most common side effects in people who take VOTRIENT include:

- diarrhea
- change in hair color

- nausea or vomiting
- loss of appetite

Other common side effects in people with advanced soft tissue sarcoma who take VOTRIENT include:

- feeling tired
- decreased weight
- tumor pain
- muscle or bone pain
- stomach pain

- headache
- taste changes
- trouble breathing
- change in skin color

These are not all the possible side effects of VOTRIENT. Call your doctor for medical advice about side effects. You may report side effects to FDA at 1-800-FDA-1088.

How should I store VOTRIENT tablets?
Store VOTRIENT at room temperature between 68°F and 77°F (20°C to 25°C).
Keep VOTRIENT and all medicines out of the reach of children.

General information about the safe and effective use of VOTRIENT.
Medicines are sometimes prescribed for purposes other than those listed in a Medication Guide. Do not use VOTRIENT for a condition for which it was not prescribed. Do not give VOTRIENT to other people even if they have the same symptoms that you have. It may harm them.
You can ask your pharmacist or healthcare provider for information about VOTRIENT that is written for healthcare professionals.

What are the ingredients in VOTRIENT?
Active ingredient: pazopanib.
Inactive ingredients: Tablet core: Magnesium stearate, microcrystalline cellulose, povidone, and sodium starch glycolate. Coating: Gray or pink film-coated tablets: Hypromellose, iron oxide black, macrogol/polyethylene glycol 400 (PEG 400), polysorbate 80, and titanium dioxide.
Distributed by: Novartis Pharmaceuticals Corporation, East Hanover, New Jersey 07936 © Novartis
For more information, go to www.VOTRIENT.com or call 1-888-669-6682.

This Medication Guide has been approved by the U.S. Food and Drug Administration.

Revised: December 2021

T2021-161

PRINCIPAL DISPLAY PANEL

NDC 0078-1077-66

Votrient®

(pazopanib)

Tablets

200 mg

120 Tablets

Rx only

Each tablet contains 216.7 mg of
pazopanib hydrochloride, equivalent
to 200 mg of pazopanib free base.

Dispense with Medication Guide
attached or provided separately.

NOVARTIS